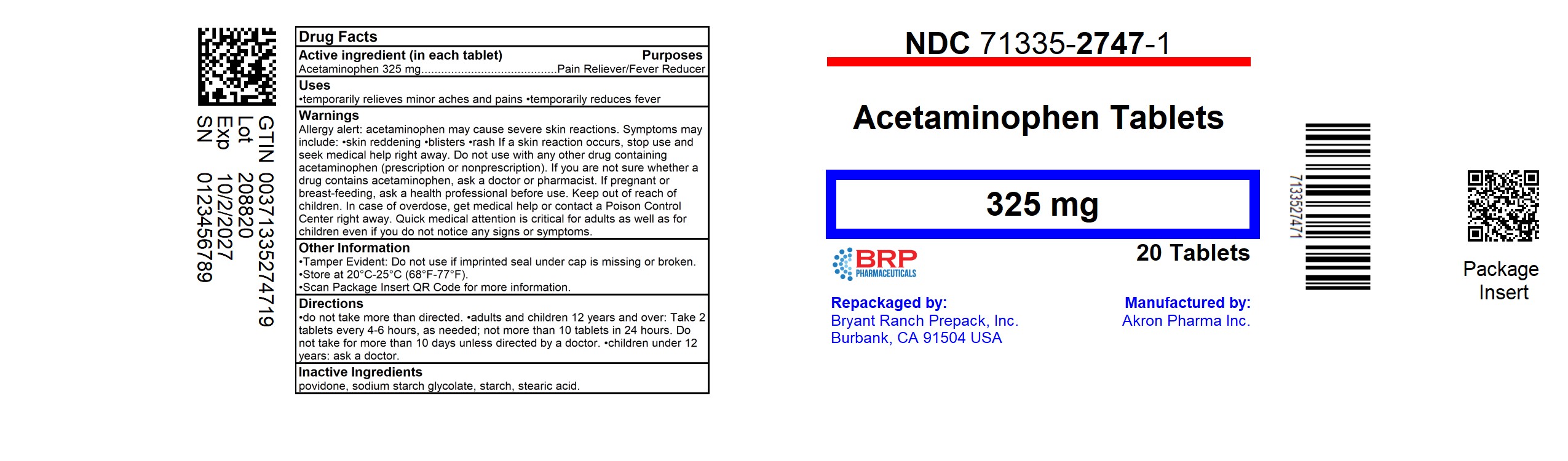 DRUG LABEL: ACETAMINOPHEN
NDC: 71335-2747 | Form: Tablet
Manufacturer: Bryant Ranch Prepack
Category: otc | Type: HUMAN OTC DRUG LABEL
Date: 20251002

ACTIVE INGREDIENTS: ACETAMINOPHEN 325 mg/1 1
INACTIVE INGREDIENTS: STARCH, CORN; MAGNESIUM STEARATE; POVIDONE, UNSPECIFIED

Acetaminophen 325 mg Tablets
Regular Strength

Active ingredient (in each tablet)

Acetaminophen 325 mg

Purpose

Pain Reliever/Fever Reducer

Uses

To reduce fever and for the temporary relief of minor aches and pains due to:

•headache

•muscular aches

•backache

•minor pain of arthritis

•the common cold

•toothache

•premenstrual and menstrual cramps.

•Temporarily reduces fever.

Warnings

Liver warning:

This product contains acetaminophen. Severe liver damage may occur if

- adult takes more than 4,000 mg of acetaminophen in 24 hours
- child takes more than 5 doses in 24 hours
- taken with other drugs containing acetaminophen
- adult has 3 or more alcoholic drinks every day while using this product

Allergy alert: Acetaminophen may cause severe skin reactions. Symptoms may include:

- skin reddening
- blisters
- rash

If a skin reaction occurs, stop use and seek medical help right away.

Do not use

- with any other drug containing acetaminophen (prescription or non-prescription). If you are not sure whether a drug contains acetaminophen, ask a doctor or pharmacist.
- if the user has ever had an allergic reaction to this product or any of its ingredients.

Ask a doctor before use if the user has

- has liver disease
- is a child with pain of arthritis

Ask a doctor or pharmacist before use if your child is taking the blood thinning drug warfarin

Stop use and ask a doctor if:

- pain gets worse or lasts more than 10 days (for adults) or 5 days (for children)
- fever gets worse or lasts more than 3 days
- new symptoms occur
- redness or swelling is present.

These could be signs of a serious condition.

PREGNANCY OR BREAST FEEDING

If pregnant or breast-feeding, ask a health professional before use.

Keep out of reach of children.

Overdose Warning:

Taking more than the recommended dose (overdose) may cause liver damage. In case of overdose, get medical help or contact a Poison Control Center right away.(1-800-222-1222)

Quick medical attention is critical for adults as well as for children even if you do not notice any signs or symptoms.

Directions - do not take more than directed (see overdose warning)

adults & children 12 years and over | - take 2 tablets every 4 to 6 hours while symptoms last - do not take more than 10 tablets in 24 hours - do not use for more than 10 days unless directed by a doctor
children 6-11 years | - take 1 tablet every 4 to 6 hours while symptoms last - do not take more than 5 tablets in 24 hours - do not use for more than 5 days unless directed by a doctor
child under 6 years | ask a doctor

Other information

- store at 20° to 25°C (68° to 77°F)

Inactive Ingredients:

Gelatinized starch, magnesium stearate, povidone

Questions or Comments?

Call toll-free 1-877-225-6999

Manufactured for
Akron Pharma, Inc.,

373 RT US46 W Building E,

Suite 117, Fairfeld, NJ - 07004

Mfg. Lic. No: TN/DRUGS/558/1997

* This product is not manufactured or distributed by Johnson and Johnson, consumer inc., distributor of regular Tylenol Tablets.

HOW SUPPLIED

Acetaminophen 325 mg tablet: white color, round shape and the imprint code is A325.

NDC: 71335-2747-1: 20 Tablets in a BOTTLE

NDC: 71335-2747-2: 100 Tablets in a BOTTLE

NDC: 71335-2747-3: 30 Tablets in a BOTTLE

NDC: 71335-2747-4: 2 Tablets in a BOTTLE

NDC: 71335-2747-5: 6 Tablets in a BOTTLE

NDC: 71335-2747-6: 10 Tablets in a BOTTLE

NDC: 71335-2747-7: 60 Tablets in a BOTTLE

NDC: 71335-2747-8: 90 Tablets in a BOTTLE

NDC: 71335-2747-9: 40 Tablets in a BOTTLE

NDC: 71335-2747-0: 24 Tablets in a BOTTLE

Store at 20° to 25°C (68° to 77°F)

Repackaged/Relabeled by:
Bryant Ranch Prepack, Inc.
Burbank, CA 91504

PACKAGE LABEL

Acetaminophen 325 mg Tablet